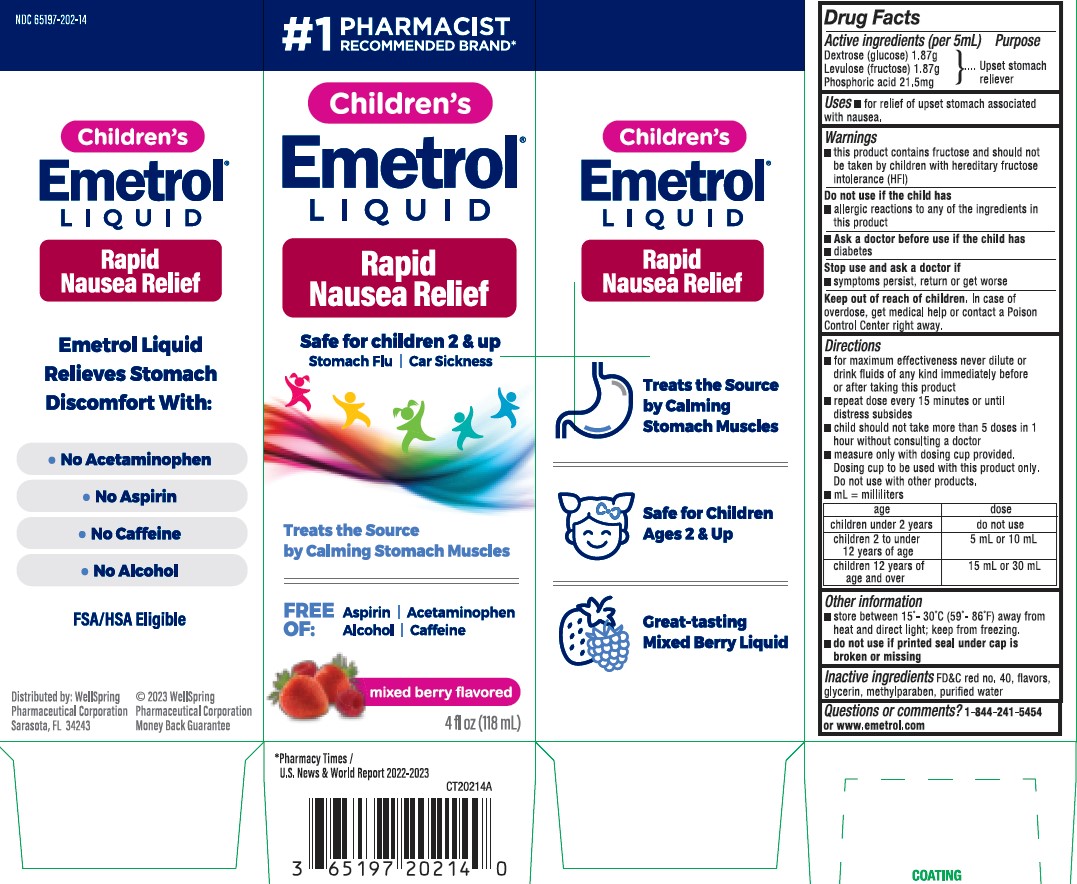 DRUG LABEL: Emetrol Children Mixed Berry
NDC: 65197-202 | Form: SOLUTION
Manufacturer: WellSpring Pharmaceutical Corporation
Category: otc | Type: HUMAN OTC DRUG LABEL
Date: 20250108

ACTIVE INGREDIENTS: DEXTROSE 1.87 g/5 mL; PHOSPHORIC ACID 21.5 mg/5 mL; FRUCTOSE 1.87 g/5 mL
INACTIVE INGREDIENTS: FD&C RED NO. 40; GLYCERIN; METHYLPARABEN; WATER

Emetrol Liquid 4oz

Active ingredients

Phosphorated carbohydrate solution*
*each 5 mL contains:

- 1.87 g Dextrose (glucose)
- 1.87 g Levulose (fructose)
- 21.5 mg Phosphoric acid

Purpose

Upset Stomach Reliever

Uses

For relief of upset stomach associated with nausea

Warnings

- This product contains fructose and should not be taken by children with hereditary fructose intolerance (HFI).

Do not use if the child has

- allergic reactions to any of the ingredients in this product

Ask a doctor before use if the child has

- diabetes

Stop use and ask a doctor if

- symptoms persist, return or get worse

Keep out of reach of children.

In case of overdose, get medical help or contact a Poison Control Center right away

Directions

- for maximum effectiveness never dilute or drink fluids of any kind immediately before or after taking this product
- repeat dose every 15 minutes or until distress subsides
- Child should not take more than 5 doses in 1 hour without consulting a doctor
- measure only with dosing cup provided. Dosing cup to be used with Emetrol only. Do not use with other products. mL= milliliter
- children under 2 years - Do not use
- children 2 to under 12 years of age - 5 mL or 10mL
- children 12 years of age and over - 15 mL or 30 mL

Other information

- Store between 20-25ºC (68-77ºF) away from heat and direct light; keep from freezing
- Do not use if printed foil seal under bottle cap is broken or missing

Inactive ingredients

FD&C red no. 40, flavors, glycerin, methylparaben, and purified water.

Questions or Comments?

call 1-844-241-5454 or www.emetrol.com

Distributed By

WellSpring Pharmaceutical Corporation
Sarasota, FL 34243 USA
(c) WellSpring 2023

Money Back Guarantee

PACKAGE LABEL

Treats the source by Calming Stomach Muscles

Safe for children Ages 2 & Up

Great-tasting Mixed Berry Liquid

Free of: Aspirin | Acetaminophen | Alcohol | Caffeine

Emetrol Children's Liquid Mixed Berry